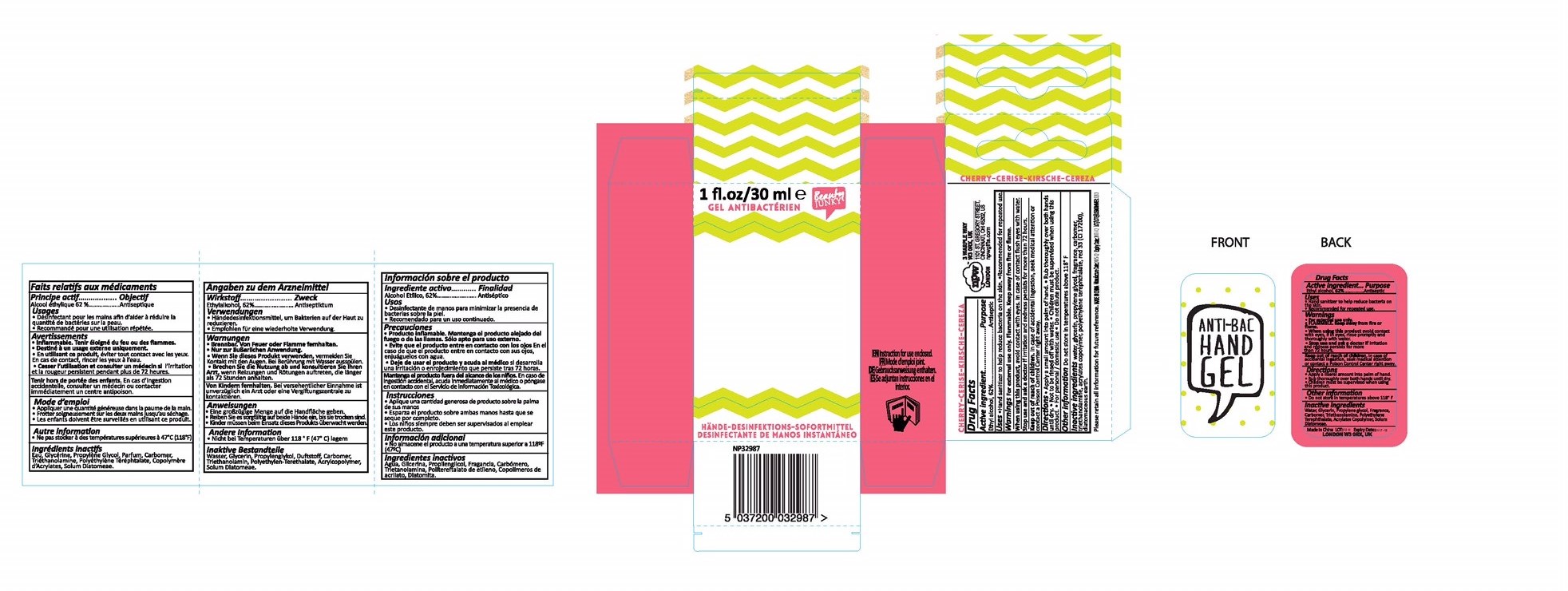 DRUG LABEL: Hand Sanitizer
NDC: 49435-001 | Form: GEL
Manufacturer: NPW-USA, Inc.
Category: otc | Type: HUMAN OTC DRUG LABEL
Date: 20160111

ACTIVE INGREDIENTS: ALCOHOL 62 mL/100 mL
INACTIVE INGREDIENTS: WATER; POLYETHYLENE TEREPHTHALATE (INTRINSIC VISCOSITY 0.70-1.00); GLYCERIN; PROPYLENE GLYCOL; CARBOMER INTERPOLYMER TYPE A (55000 CPS); TROLAMINE; D&C RED NO. 33; METHACRYLIC ACID - ETHYL ACRYLATE COPOLYMER (4500 MPA.S); DIATOMACEOUS EARTH

Active ingredient:
Ethyl alcohol, 62%

Purpose Antiseptic

Warnings:

For external use only.

FLAMMBLE. Keep away from fire or flame.

Stop use and ask a doctor if irritation and redness persists for more than 72 hours.

Keep out of reach of children. In case of accidental ingestion, seek medical attention or contact a Poison Control Center right away.

Directions:

- Apply a small amount into palm of hand
- Rub thoroughly over both hands until dry
- Not to be rinsed off with water
- Children must be supervised when using this product
- For personal / domestic use
- Do not dilute product

INACTIVE INGREDIENT

Inactive ingredients: water, glycerin, propylene glycol, fragrance, carbomer, triethanolamine, acrylates copolymer, polyethylene terephthalate, red 33, diatomaceous earth.

Other Information:

Do not store in temperatures above 118 F

Uses:

- Hand sanitizer to help reduce bacteria on the skin.
- Recommended for repeated use.

When using this product, avoid contact with eyes. In case of contact flush eyes with water.